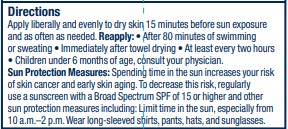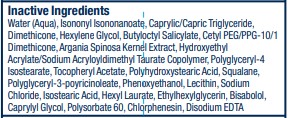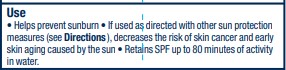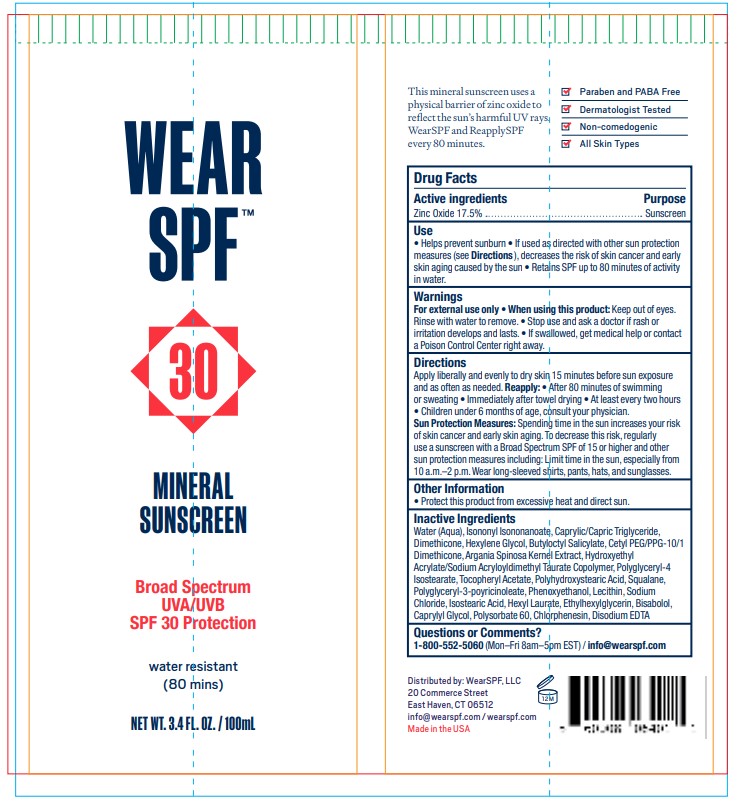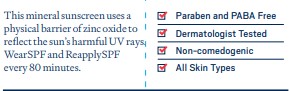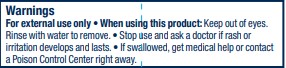 DRUG LABEL: Antioxidant Mineral Sunscreen SPF30
NDC: 57577-681 | Form: LOTION
Manufacturer: Milbar Laboratories
Category: otc | Type: HUMAN OTC DRUG LABEL
Date: 20240729

ACTIVE INGREDIENTS: ZINC OXIDE 20.055 g/100 mL
INACTIVE INGREDIENTS: POLYHYDROXYSTEARIC ACID (2300 MW); ISOSTEARIC ACID; HEXYL LAURATE; MEDIUM-CHAIN TRIGLYCERIDES; LEVOMENOL; POLYSORBATE 60; EDETATE DISODIUM; CHLORPHENESIN; POLYGLYCERYL-3 RICINOLEATE; HEXYLENE GLYCOL; POLYGLYCERYL-4 ISOSTEARATE; ISONONYL ISONONANOATE; CETYL PEG/PPG-10/1 DIMETHICONE (HLB 2); HYDROXYETHYL ACRYLATE/SODIUM ACRYLOYLDIMETHYL TAURATE COPOLYMER (45000 MPA.S AT 1%); ARGAN OIL; SQUALANE; SODIUM CHLORIDE; .ALPHA.-TOCOPHEROL ACETATE; PHENOXYETHANOL; LECITHIN, SOYBEAN; ETHYLHEXYLGLYCERIN; CAPRYLYL GLYCOL; WATER; DIMETHICONE; BUTYLOCTYL SALICYLATE

Antioxidant Mineral Sunscreen SPF30